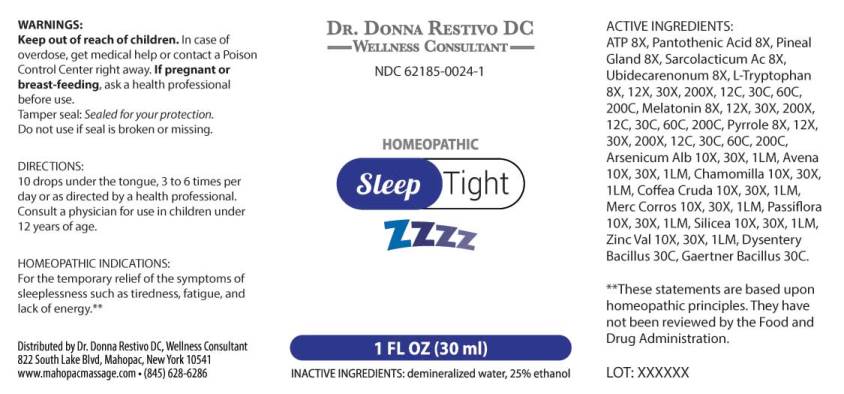 DRUG LABEL: Sleep Tight
NDC: 62185-0024 | Form: LIQUID
Manufacturer: Dr. Donna Restivo DC
Category: homeopathic | Type: HUMAN OTC DRUG LABEL
Date: 20240118

ACTIVE INGREDIENTS: ADENOSINE TRIPHOSPHATE DISODIUM 8 [hp_X]/1 mL; PANTOTHENIC ACID 8 [hp_X]/1 mL; SUS SCROFA PINEAL GLAND 8 [hp_X]/1 mL; LACTIC ACID, L- 8 [hp_X]/1 mL; UBIDECARENONE 8 [hp_X]/1 mL; TRYPTOPHAN 8 [hp_X]/1 mL; MELATONIN 8 [hp_X]/1 mL; PYRROLE 8 [hp_X]/1 mL; ARSENIC TRIOXIDE 10 [hp_X]/1 mL; AVENA SATIVA FLOWERING TOP 10 [hp_X]/1 mL; MATRICARIA CHAMOMILLA WHOLE 10 [hp_X]/1 mL; ARABICA COFFEE BEAN 10 [hp_X]/1 mL; MERCURIC CHLORIDE 10 [hp_X]/1 mL; PASSIFLORA INCARNATA FLOWERING TOP 10 [hp_X]/1 mL; SILICON DIOXIDE 10 [hp_X]/1 mL; ZINC VALERATE DIHYDRATE 10 [hp_X]/1 mL; SHIGELLA DYSENTERIAE 30 [hp_C]/1 mL; SALMONELLA ENTERICA SUBSP. ENTERICA SEROVAR ENTERITIDIS 30 [hp_C]/1 mL
INACTIVE INGREDIENTS: WATER; ALCOHOL

DRUG FACTS:

ACTIVE INGREDIENTS:

Adenosinum Triphosphoricum Dinatrum 8X, Pantothenic Acid 8X, Pineal Gland (Suis) 8X, Sarcolacticum Acidum 8X, Ubidecarenonum 8X, L-Tryptophan 8X, 12X, 30X, 200X, 12C, 30C, 60C, 200C, Melatonin 8X, 12X, 30X, 200X, 12C, 30C, 60C, 200C, Pyrrole 8X, 12X, 30X, 200X, 12C, 30C, 60C, 200C, Arsenicum Album 10X, 30X, 1LM, Avena Sativa 10X, 30X, 1LM, Chamomilla 10X, 30X, 1LM, Coffea Cruda 10X, 30X, 1LM, Mercurius Corrosivus 10X, 30X, 1LM, Passiflora Incarnata 10X, 30X, 1LM, Silicea 10X, 30X, 1LM, Zincum Valerianicum 10X, 30X, 1LM, Dysentery Bacillus 30C, Gaertner Bacillus (Bach) 30C.

HOMEOPATHIC INDICATIONS:

For the temporary relief of sleeplessness such as tiredness, fatigue, and lack of energy.**

**These statements are based upon homeopathic principles. They have not been reviewed by the Food and Drug Administration.

WARNINGS:

Keep out of reach of children. In case of overdose, get medical help or contact a Poison Control Center right away.

If pregnant or breast-feeding, ask a health professional before use.

Tamper seal: Sealed for your protection.

Do not use if seal is broken or missing.

Keep out of reach of children. In case of overdose, get medical help or contact a Poison Control Center right away.

DIRECTIONS:

10 drops under the tongue, 3 to 6 times per day or as directed by a health professional. Consult a physician for use in children under 12 years of age.

HOMEOPATHIC INDICATIONS:

For the temporary relief of sleeplessness such as tiredness, fatigue, and lack of energy.**

**These statements are based upon homeopathic principles. They have not been reviewed by the Food and Drug Administration.

INACTIVE INGREDIENTS:

demineralized water, 25% ethanol

QUESTIONS:

Distributed by Dr. Donna Restivo DC, Wellness Consultant

822 South Lake Blvd. Mahopac, New York 10541

www.mahopacmassage.com • (845) 628-6286

PACKAGE LABEL DISPLAY:

DR. DONNA RESTIVO DC

WELLNESS CONSULTANT

NDC 62185-0024-1

HOMEOPATHIC

Brain SUPPORT

1 FL OZ (30 ml)